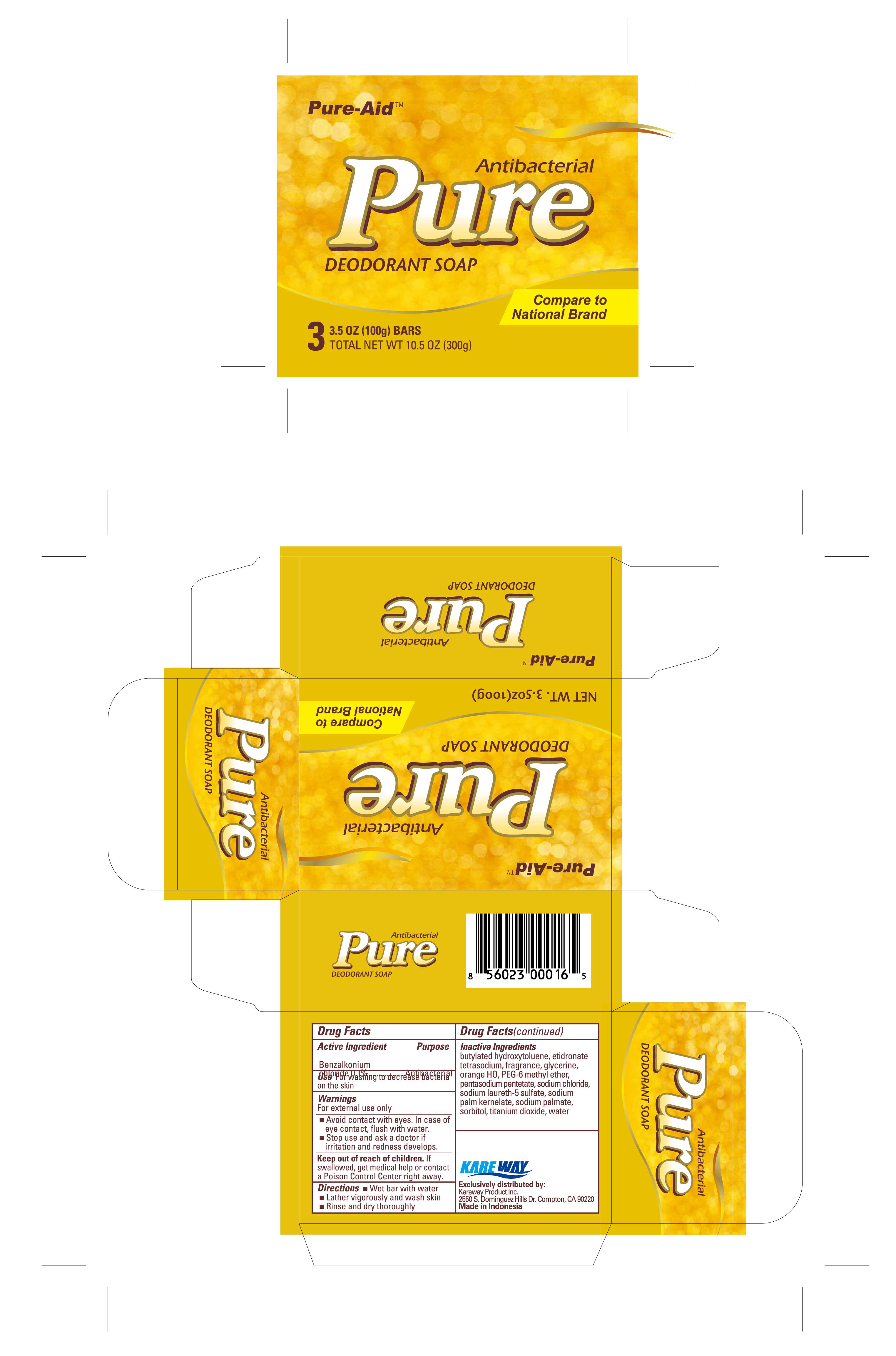 DRUG LABEL: Antibacterial Gold
NDC: 67510-0116 | Form: SOAP
Manufacturer: Kareway Product, Inc.
Category: otc | Type: HUMAN OTC DRUG LABEL
Date: 20200722

ACTIVE INGREDIENTS: BENZALKONIUM CHLORIDE 0.1 g/100 g
INACTIVE INGREDIENTS: GLYCERIN; PALMITIC ACID; PEG-6 METHYL ETHER; PENTASODIUM PENTETATE; SODIUM CHLORIDE; SODIUM PALMITATE; SODIUM PALM KERNELATE; SORBITOL; ETIDRONATE TETRASODIUM; WATER; BUTYLATED HYDROXYTOLUENE; TITANIUM DIOXIDE; FD&C YELLOW NO. 6

Pure-Aid Antibacterial Soap Gold

Active Ingredient

Benzalkonium Chloride 0.1%

Purpose

Antibacterial

Use

For washing to decrease bacteria on the skin

Warnings

For external use only

- Avoid contact with eyes. In case of eye contact, flush with water.
- Stop use and ask a doctor if irritation and redness develops.

Keep out of reach of children.

If swallowed, get medical help or contact a Poison Control Center right away.

Directions

- Wet bar with water
- Lather vigorously and wash skin
- Rinse and dry thoroghly

Inactive Ingredient

butylated hydroxytoluene, etidronate tetrasodium, fragrance, glycerine, orange HO, PEG-6 methyl ether, pentasodium pentetate, sodium chloride, sodium laureth-5 sulfate, sodium palm kernelate, sodium palmate, sorbitol, titanium dioxide, water